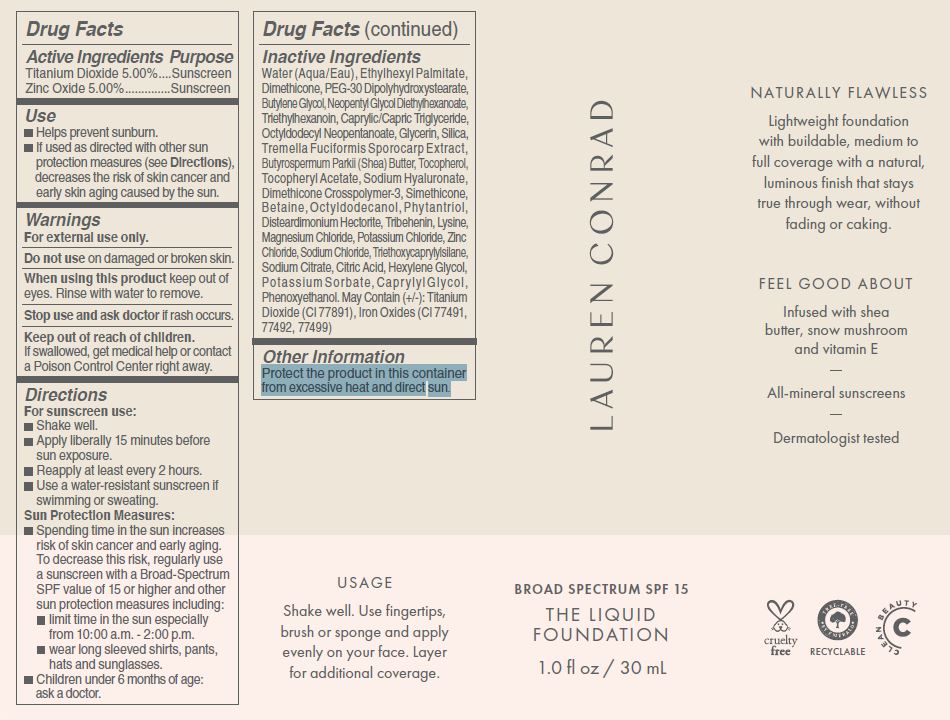 DRUG LABEL: LC FOUNDATION SPF 15
NDC: 59735-401 | Form: CREAM
Manufacturer: MANA Products INC.
Category: otc | Type: HUMAN OTC DRUG LABEL
Date: 20240103

ACTIVE INGREDIENTS: TITANIUM DIOXIDE 5 g/100 g; ZINC OXIDE 5 g/100 g
INACTIVE INGREDIENTS: DISTEARDIMONIUM HECTORITE; LYSINE; ZINC CHLORIDE; HEXYLENE GLYCOL; FERROSOFERRIC OXIDE; BUTYLENE GLYCOL; TRIETHYLHEXANOIN; ETHYLHEXYL PALMITATE; DIMETHICONE; SILICON DIOXIDE; PHENOXYETHANOL; TREMELLA FUCIFORMIS FRUITING BODY; TOCOPHEROL; DIMETHICONE CROSSPOLYMER (450000 MPA.S AT 12% IN CYCLOPENTASILOXANE); BETAINE; OCTYLDODECANOL; PHYTANTRIOL; TRIBEHENIN; SODIUM CHLORIDE; SODIUM CITRATE; WATER; PEG-30 DIPOLYHYDROXYSTEARATE (5000 MW); NEOPENTYL GLYCOL DIETHYLHEXANOATE; MEDIUM-CHAIN TRIGLYCERIDES; OCTYLDODECYL NEOPENTANOATE; GLYCERIN; SHEA BUTTER; ALPHA-TOCOPHEROL ACETATE; HYALURONATE SODIUM; MAGNESIUM CHLORIDE; POTASSIUM CHLORIDE; TRIETHOXYCAPRYLYLSILANE; ANHYDROUS CITRIC ACID; POTASSIUM SORBATE; CAPRYLYL GLYCOL

LC FOUNDATION SPF 15

ACTIVE INGREDIENTS

Titanium Dioxide 5.00%

Zinc Oxide 5.00%

PURPOSE

SUNSCREEN

USES

-Helps prevent sunburn.
-If used as directed with other sun protection measures (see Directions), decreases the risk of skin cancer and early skin aging caused by the sun.

WARNINGS

For external use only.

Do not use on damaged or broken skin.

When using this product keep out of eyes. Rinse with water to remove.

DIRECTIONS

For sunscreen use:

Shake well.
Apply liberally 15 minutes before sun exposure.
Reapply at least every 2 hours.
Use a water-resistant sunscreen if swimming or sweating.

Sun Protection Measures:

Spending time in the sun increases risk of skin cancer and early aging. To decrease this risk, regularly use a sunscreen with a Broad-Spectrum SPF value of 15 or higher and other sun protection measures including:
limit time in the sun especially from 10:00 a.m. - 2:00 p.m.
wear long sleeved shirts, pants, hats and sunglasses.
Children under 6 months of age: ask a doctor.

INACTIVE INGREDIENTS

Water (Aqua/Eau), Ethylhexyl Palmitate, Dimethicone, PEG-30 Dipolyhydroxystearate, Butylene Glycol, Neopentyl Glycol Diethylhexanoate, Triethylhexanoin, Caprylic/Capric Triglyceride, Octyldodecyl Neopentanoate, Glycerin, Silica, Tremella Fuciformis Sporocarp Extract, Butyrospermum Parkii (Shea) Butter, Tocopherol, Tocopheryl Acetate, Sodium Hyaluronate, Dimethicone Crosspolymer-3, Simethicone, Betaine, Octyldodecanol, Phytantriol, Disteardimonium Hectorite, Tribehenin, Lysine, Magnesium Chloride, Potassium Chloride, Zinc Chloride, Sodium Chloride, Triethoxycaprylylsilane, Sodium Citrate, Citric Acid, Hexylene Glycol, Potassium Sorbate, Capr ylyl Glycol, Phenoxyethanol. May Contain (+/-): Titanium Dioxide (CI 77891), Iron Oxides (CI 77491, 77492, 77499)

Stop use and ask a doctor if rash occurs.

RECENT MAJOR CHANGES

Dosage & Admin update

Keep out of reach of children. If product is swallowed, get medical help or contact a Poison Control Center right away.